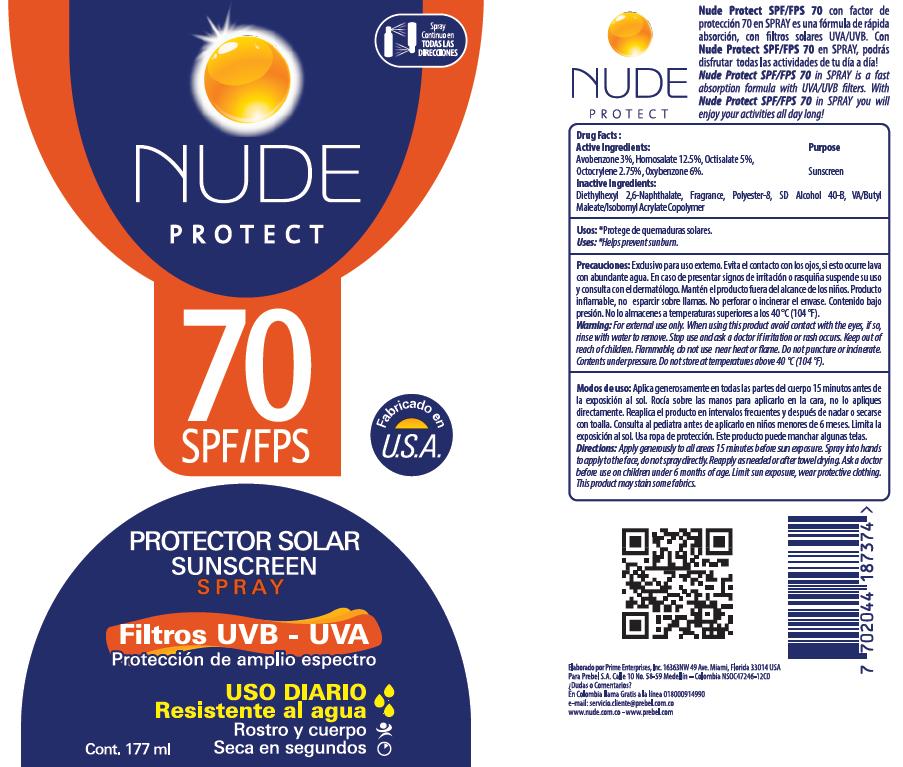 DRUG LABEL: Prebel
NDC: 13630-0096 | Form: SPRAY
Manufacturer: Prime Packaging Inc.
Category: otc | Type: HUMAN OTC DRUG LABEL
Date: 20200117

ACTIVE INGREDIENTS: AVOBENZONE 25.6 mg/1 mL; HOMOSALATE 106.5 mg/1 mL; OCTISALATE 42.6 mg/1 mL; OCTOCRYLENE 23.43 mg/1 mL; OXYBENZONE 51.12 mg/1 mL
INACTIVE INGREDIENTS: ALCOHOL; DIETHYLHEXYL 2,6-NAPHTHALATE; POLYESTER-8 (1400 MW, CYANODIPHENYLPROPENOYL CAPPED); DIBUTYL MALEATE

Nude Protect SPF 70 Sunscreen Spray

Active Ingredients

Avobenzone 3%

Homosalate 12.5%

Octisalate 5%

Octocrylene 2.75%

Oxybenzone 6%

PURPOSE

Sunscreen

INACTIVE INGREDIENT

Diethylhexyl 2,6-Napthalate, Fragrance, Polyester-8, SD Alcohol 40-B, VA/Butyl Maleate/Isobornyl Acrylate Copolymer

Uses

*Helps prevent sunburn

WARNINGS

For external use only. When using thi sproduct avoid contact with eyes, if so, rinse with water to remove. Stop use and ask a doctor if irritation or rash occurs. Keep out of reach of children. Flammable, do not use near heat or flame. Do not puncture or incinerate. Contents under pressure. Do not store at temperatures above 40ºC (104 ºF).

Directions

Apply generously to all areas 15 minutes before sun exposure. Spray into hands to apply to face, do not spray directly. Reapply as needed or after towel drying. Ask a doctor before use on children under 6 months of age. Limit sun exposure, wear protective clothing. This product may stain some fabrics.